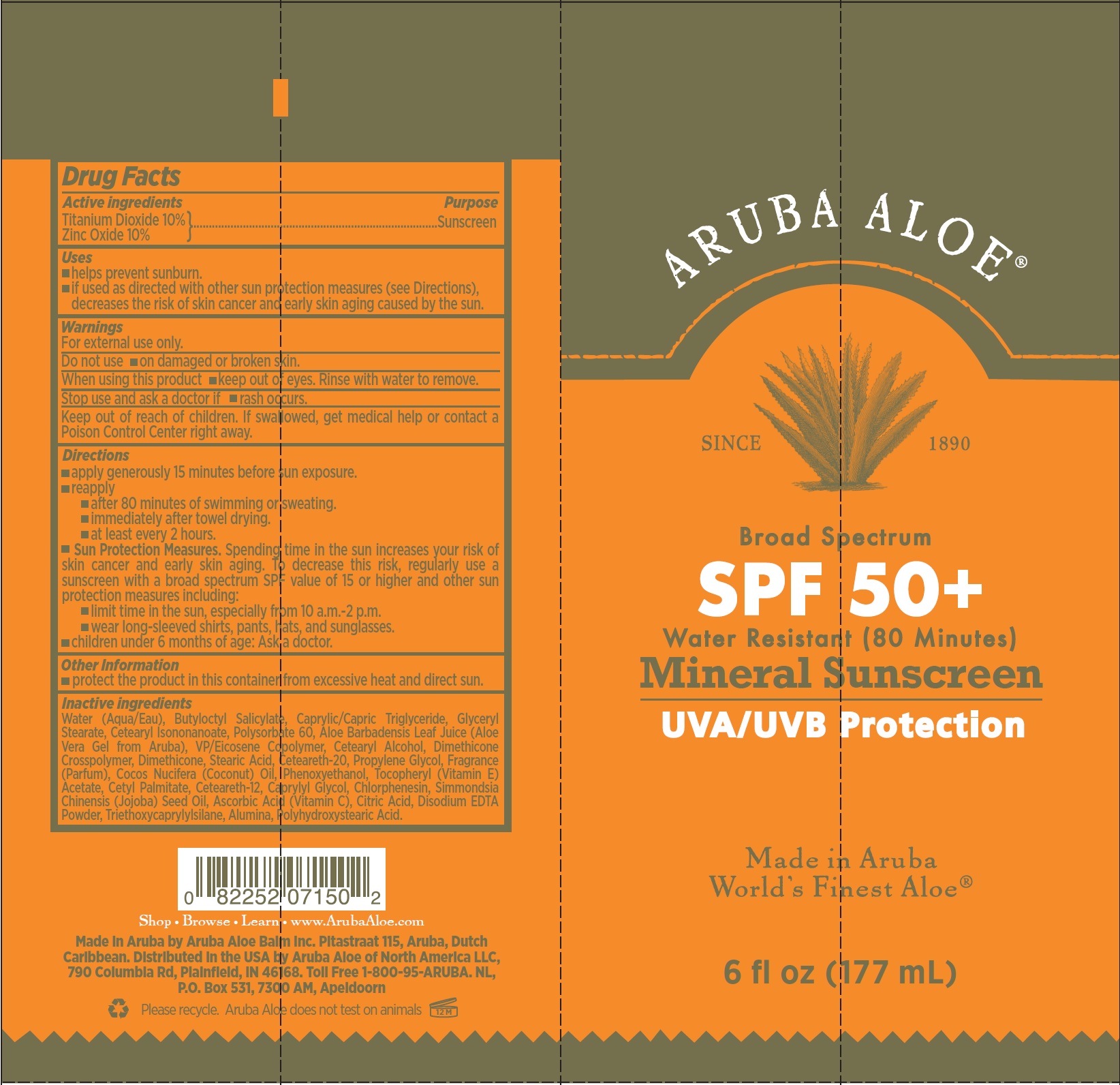 DRUG LABEL: Aruba Aloe SPF 50 Mineral Sunscreen
NDC: 53675-194 | Form: CREAM
Manufacturer: Aruba Aloe Balm NV
Category: otc | Type: HUMAN OTC DRUG LABEL
Date: 20231106

ACTIVE INGREDIENTS: TITANIUM DIOXIDE 100 mg/1 mL; ZINC OXIDE 100 mg/1 mL
INACTIVE INGREDIENTS: WATER; BUTYLOCTYL SALICYLATE; MEDIUM-CHAIN TRIGLYCERIDES; GLYCERYL MONOSTEARATE; CETEARYL ISONONANOATE; POLYSORBATE 60; ALOE VERA LEAF; CETOSTEARYL ALCOHOL; DIMETHICONE; STEARIC ACID; POLYOXYL 20 CETOSTEARYL ETHER; PROPYLENE GLYCOL; COCONUT OIL; PHENOXYETHANOL; .ALPHA.-TOCOPHEROL ACETATE; CETYL PALMITATE; CETEARETH-12; CAPRYLYL GLYCOL; CHLORPHENESIN; JOJOBA OIL; ASCORBIC ACID; CITRIC ACID MONOHYDRATE; EDETATE DISODIUM ANHYDROUS; TRIETHOXYCAPRYLYLSILANE; ALUMINUM OXIDE; POLYHYDROXYSTEARIC ACID (2300 MW)

Aruba Aloe SPF 50+ Mineral Sunscreen

Active ingredients

Titanium Dioxide 10% Zinc Oxide 10%

Purpose

Sunscreen

Uses

- helps prevent sunburn.
- if used as directed with other sun protection measures (see Directions), decreases the risk of skin cancer and early skin aging caused by the sun.

Warnings

For external use only.

Do not use

- on damaged or broken skin.

When using this product

- keep out of eyes. Rinse with water to remove.

Stop use and ask a doctor if

- rash occurs.

Keep out of reach of children.

If swallowed, get medical help or contact a Poison Control Center right away.

Directions

- apply generously 15 minutes before sun exposure.
- reapply
- after 80 minutes of swimming or sweating.
- immediately after towel drying.
- at least every 2 hours.
- Spending time in the sun increases your risk of skin cancer and early skin aging. To decrease this risk, regularly use a sunscreen with a broad spectrum SPF value of 15 or higher and other sun protection measures including: Sun Protection Measures.
- limit time in the sun, especially from 10 a.m.-2 p.m.
- wear long-sleeved shirts, pants, hats, and sunglasses.
- children under 6 months of age: Ask a doctor.

Other Information

- protect the product in this container from excessive heat and direct sun.

Inactive ingredients

Water (Aqua/Eau), Butyloctyl Salicylate, Caprylic/Capric Triglyceride, Glyceryl Stearate, Cetearyl Isononanoate, Polysorbate 60, Aloe Barbadensis Leaf Juice (Aloe Vera Gel from Aruba), VP/Eicosene Copolymer, Cetearyl Alcohol, Dimethicone Crosspolymer, Dimethicone, Stearic Acid, Ceteareth-20, Propylene Glycol, Fragrance (Parfum), Cocos Nucifera (Coconut) Oil, Phenoxyethanol, Tocopheryl (Vitamin E) Acetate, Cetyl Palmitate, Ceteareth-12, Caprylyl Glycol, Chlorphenesin, Simmondsia Chinensis (Jojoba) Seed Oil, Ascorbic Acid (Vitamin C), Citric Acid, Disodium EDTA Powder, Triethoxycaprylylsilane, Alumina, Polyhydroxystearic Acid.